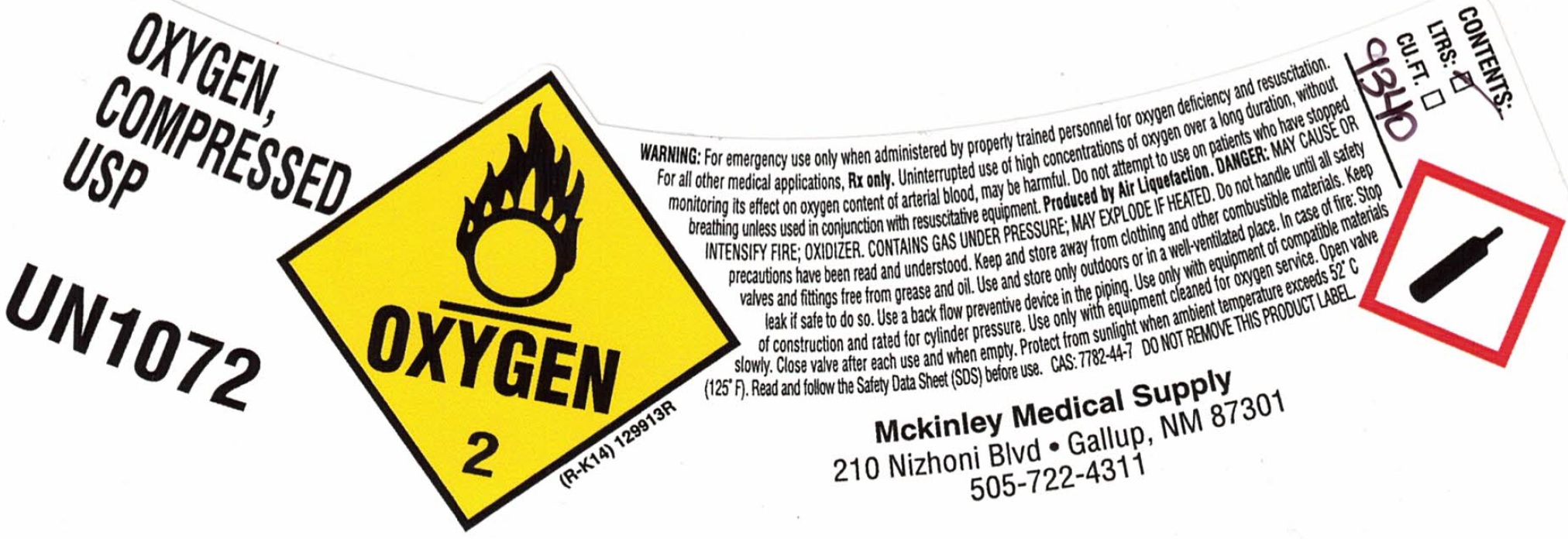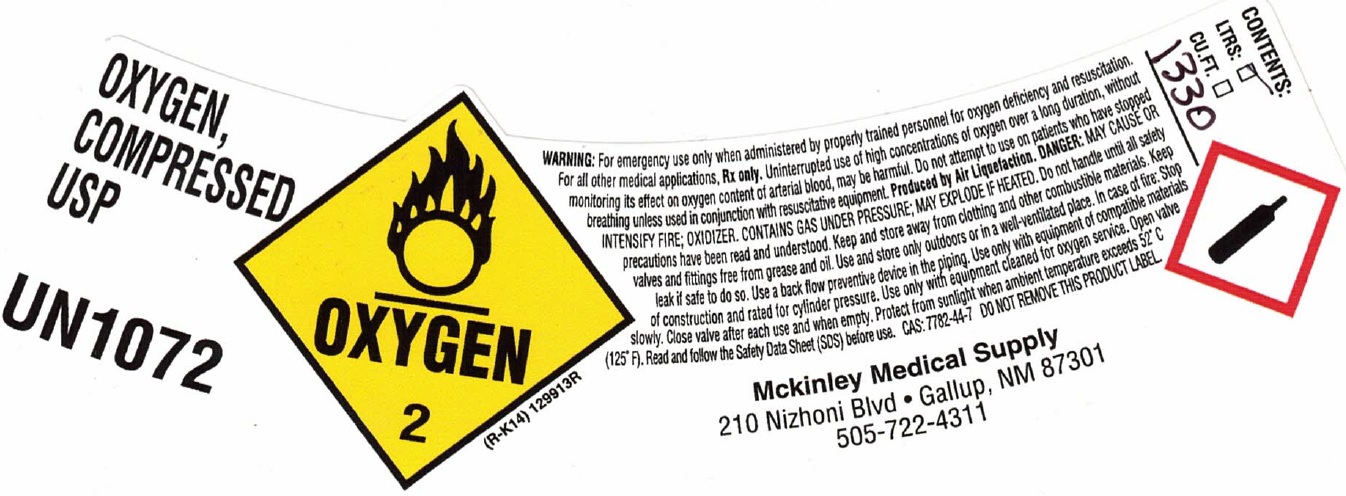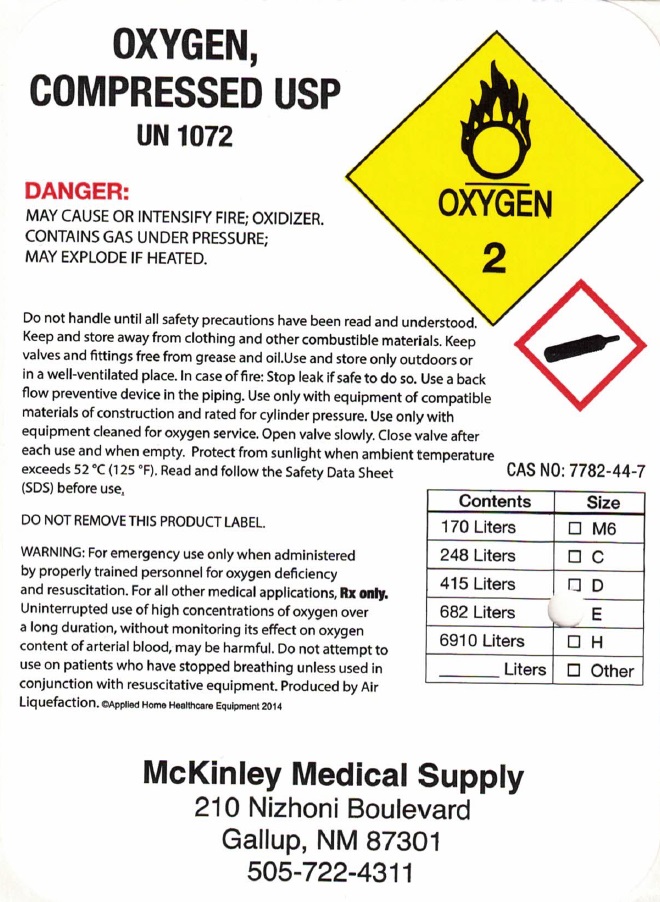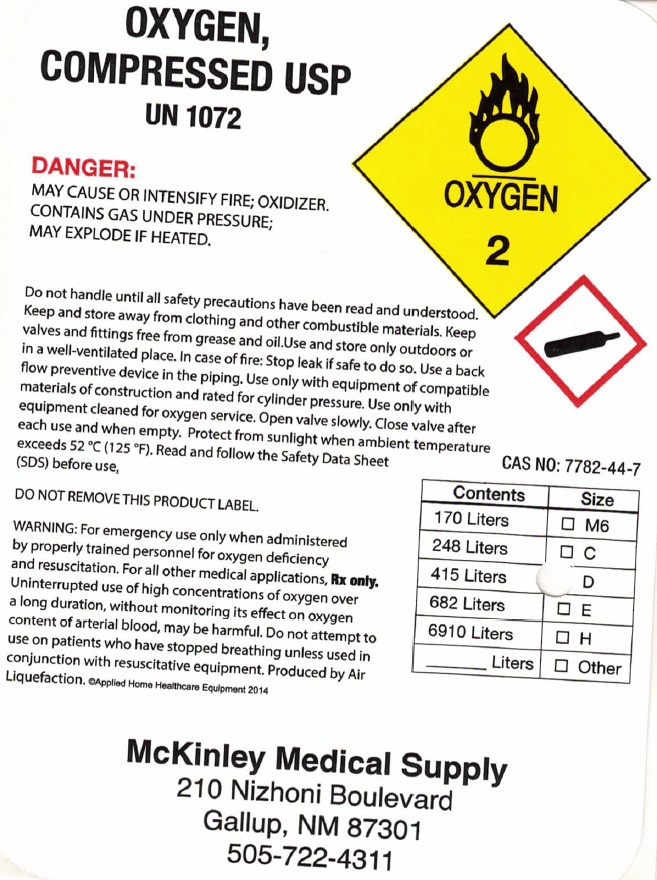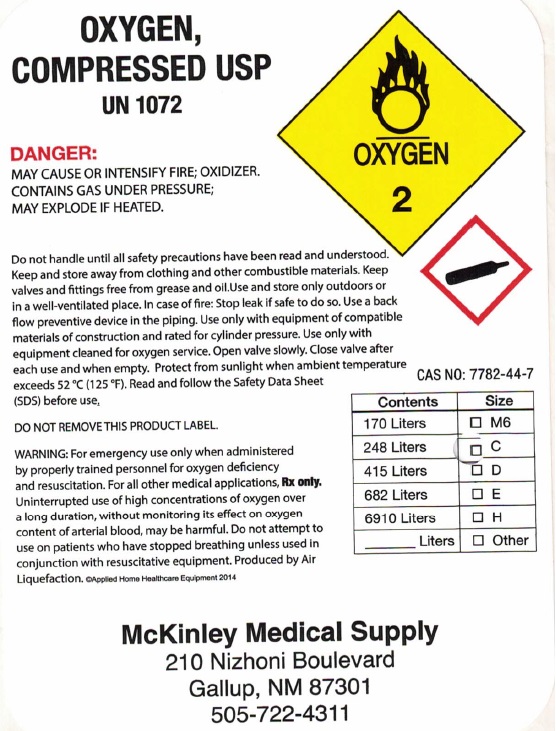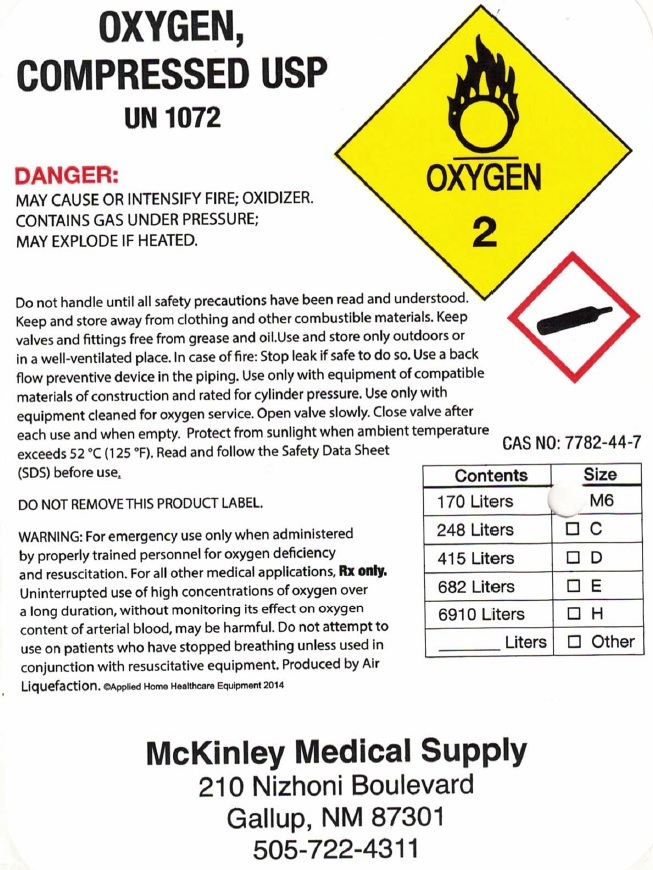 DRUG LABEL: Medical Gasseous Oxygen Cylinders
NDC: 64304-4304 | Form: GAS
Manufacturer: McKinley Medical Supply, Inc.
Category: prescription | Type: HUMAN PRESCRIPTION DRUG LABEL
Date: 20240411

ACTIVE INGREDIENTS: OXYGEN 1 L/1 L

Medical Gasseous Oxygen Cylinders